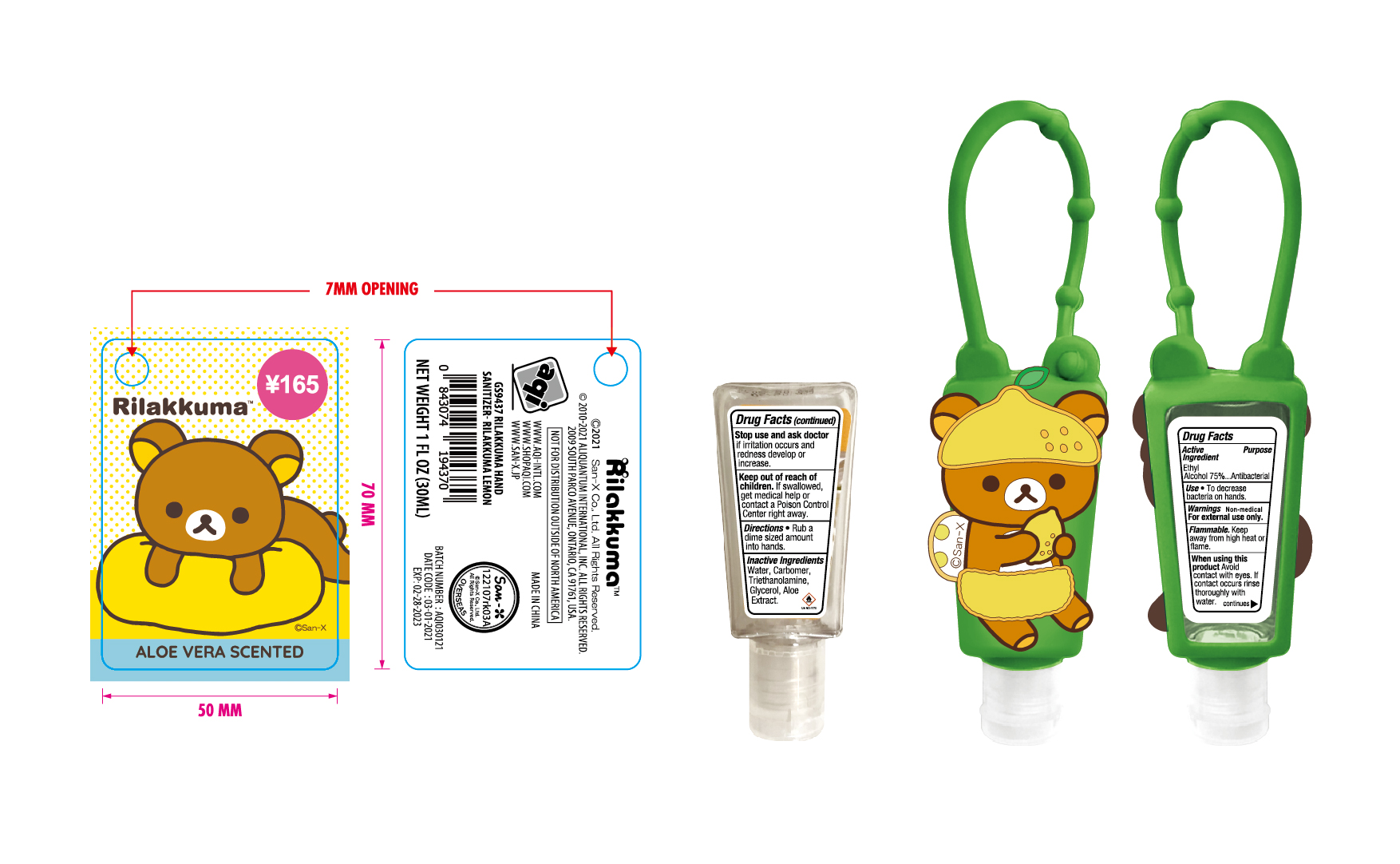 DRUG LABEL: Rilakkuma Aloe Vera Scented
NDC: 73027-216 | Form: GEL
Manufacturer: JIANGSU HANHE DAILY CHEMICALS CO., LTD.
Category: otc | Type: HUMAN OTC DRUG LABEL
Date: 20230315

ACTIVE INGREDIENTS: ALCOHOL 75 mL/100 mL
INACTIVE INGREDIENTS: CARBOMER 940; TROLAMINE; GLYCEROL FORMAL; ALOE VERA LEAF

73027-216
JIANGSU HANHE DAILY CHEMICALS CO., LTD

ACTIVE INGREDIENT

Ethyl Alcohol 75%

Purpose

Antibacterial

Use

To decrease bateria on hands

Warnings

For external use only.

Non Medical. Flammable. Keep away from high heat or flame

When using this product, avoid contact with eyes. If contact occurs, rinse thoroughly with water

Stop use and ask doctor if irritation occurs and redness develops or increases.

Keep out of reach of children. If swallowed, get medical help or contact a poison control center right away

Directions

- Rub a dime sied amount into hands

Inactive ingredients

Water, Carbomer, Triethanolamine, Glycerol, Aloe Extract